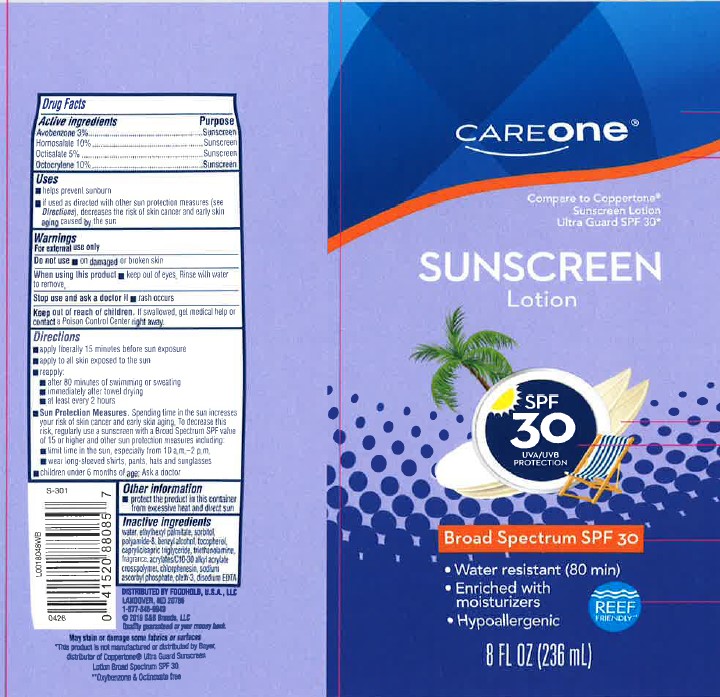 DRUG LABEL: Sunscreen
NDC: 41520-769 | Form: LOTION
Manufacturer: American Sales Company
Category: otc | Type: HUMAN OTC DRUG LABEL
Date: 20260206

ACTIVE INGREDIENTS: OCTISALATE 50 mg/1 mL; OCTOCRYLENE 100 mg/1 mL; AVOBENZONE 30 mg/1 mL; HOMOSALATE 100 mg/1 mL
INACTIVE INGREDIENTS: WATER; ETHYLHEXYL PALMITATE; SORBITOL; POLYAMIDE-8 (4500 MW); BENZYL ALCOHOL; TOCOPHEROL; MEDIUM-CHAIN TRIGLYCERIDES; TROLAMINE; CARBOMER INTERPOLYMER TYPE A (ALLYL SUCROSE CROSSLINKED); CHLORPHENESIN; SODIUM ASCORBYL PHOSPHATE; OLETH-3; EDETATE DISODIUM ANHYDROUS

Care One 769.000/769AA
Ultra Sunscreen Lotion SPF 30

Active Ingredients

Avobenzone 3%

Homosalate 10%

Octisalate 5%

Octocrylene 10%

Purpose

Sunscreen

Uses

- helps prevent sunburn
- if used as directed with other sun protections measures (see Directions), decreases the risk of skin cancer and early skin aging caused by the sun

Warnings

For external use only

Do not use

- on damaged or broken skin

When using this product

- keep out of eyes. Rinse with water to remove

Stop use and ask a doctor if

- rash occurs

Keep out of reach of children

if swallowed, get medical help or contact a Poison Control Center right away.

Directions

- apply liberally 15 minutes before sun exposure
- reapply:
- after 80 minutes of swimming or sweating
- immediately after towel drying
- at least every 2 hours
- Sun Protection Measures. Spending time in the sun increases your risk of skin cancer and early skin aging. To decrease this risk, regularly use a sunscreen with a Broad Spectrum SPF value of 15 or higher and other sun protection measures including:
- limit time in the sun, especiallyu from 10 a.m. - 2 p.m.
- wear long-sleeved shirts, pants, hats and sunglasses
- children under 6 months of age: Ask a doctor

Other Information

- Protect the product in this container from excessive heat and direct sun

Inactive ingredients

water, ethylhexyl palmitate, sorbitol, polyamide-8, benzyl alcohol, tocopherol, caprylic/capric triglyceride, triethanolamine, fragrance, acrylates/C10-30 alkyl acrylate crosspolymer, chlorphenesin, sodium ascorbyl phosphate, olethe-3, disodium EDTA

ADVERSE REACTION

Distributed by Foodhold USA, LLC

Landover, MD 20785

1-877-849-9949

(C) 2019 S&S Brands, LLC

Quality guaranteed your your money back.

May stain or damage some fabrics or surfaces.

*This product is not manufacured or distribued by Bayer, distributor of Coppertone Ultra Guard Sunscreen Lotion Broad Spectrum SPF 30.

**Oxybenzone & Octinoxate free

principal display panel

Care One

Compare to Coppertone Ultra Guard Sunscreen Lotion SPF 30*

Sunscreen

Lotion

SPF 30 UVA/UVB Protection

BROAD SPECTRUM SPF 30

- Water resistant (80 minutes)
- Enriched with moisturizers
- Hypoallergenic

REEF FRIENDLY**

8 FL OZ (236 mL)